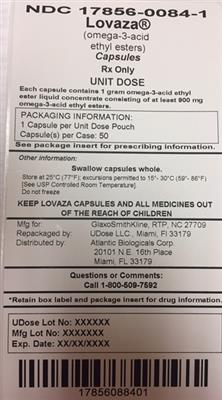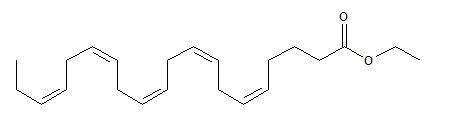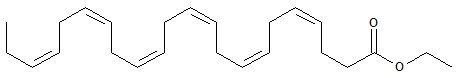 DRUG LABEL: LOVAZA
NDC: 17856-0084 | Form: CAPSULE, LIQUID FILLED
Manufacturer: Atlantic Biologicals Corps
Category: prescription | Type: HUMAN PRESCRIPTION DRUG LABEL
Date: 20161201

ACTIVE INGREDIENTS: OMEGA-3-ACID ETHYL ESTERS 900 mg/1 1
INACTIVE INGREDIENTS: .ALPHA.-TOCOPHEROL; GELATIN; GLYCERIN; WATER

HIGHLIGHTS OF PRESCRIBING INFORMATION

These highlights do not include all the information needed to use LOVAZA safely and effectively. See full prescribing information for LOVAZA.
LOVAZA® (omega-3-acid ethyl esters) capsules, for oral use
Initial U.S. Approval: 2004

1 INDICATIONS AND USAGE

LOVAZA is a combination of ethyl esters of omega 3 fatty acids, principally EPA and DHA, indicated as an adjunct to diet to reduce triglyceride (TG) levels in adult patients with severe (≥500 mg/dL) hypertriglyceridemia (HTG). (1)

Limitations of Use:

- The effect of LOVAZA on the risk for pancreatitis has not been determined. (1)
- The effect of LOVAZA on cardiovascular mortality and morbidity has not been determined. (1)

2 DOSAGE AND ADMINISTRATION

- The daily dose of LOVAZA is 4 grams per day taken as a single 4-gram dose (4 capsules) or as two 2-gram doses (2 capsules given twice daily). (2)
- Patients should be advised to swallow LOVAZA capsules whole. Do not break open, crush, dissolve, or chew LOVAZA. (2)

3 DOSAGE FORMS AND STRENGTHS

Capsules: 1 gram (3)

4 CONTRAINDICATIONS

LOVAZA is contraindicated in patients with known hypersensitivity (e.g., anaphylactic reaction) to LOVAZA or any of its components. (4)

5 WARNINGS AND PRECAUTIONS

- In patients with hepatic impairment, monitor ALT and AST levels periodically during therapy. (5.1)
- LOVAZA may increase levels of LDL. Monitor LDL levels periodically during therapy. (5.1)
- Use with caution in patients with known hypersensitivity to fish and/or shellfish. (5.2)
- There is a possible association between LOVAZA and more frequent recurrences of symptomatic atrial fibrillation or flutter in patients with paroxysmal or persistent atrial fibrillation, particularly within the first months of initiating therapy. (5.3)

6 ADVERSE REACTIONS

The most common adverse reactions (incidence >3% and greater than placebo) were eructation, dyspepsia, and taste perversion. (6)

To report SUSPECTED ADVERSE REACTIONS, contact GlaxoSmithKline at 1-888-825-5249 or FDA at 1-800-FDA-1088 or www.fda.gov/medwatch

7 DRUG INTERACTIONS

Omega-3-acids may prolong bleeding time. Patients taking LOVAZA and an anticoagulant or other drug affecting coagulation (e.g., anti-platelet agents) should be monitored periodically. (7.1)

8 USE IN SPECIFIC POPULATIONS

- Pregnancy: Use during pregnancy only if the potential benefit justifies the potential risk to the fetus. (8.1)

FULL PRESCRIBING INFORMATION

1 INDICATIONS AND USAGE

LOVAZA® (omega-3-acid ethyl esters) is indicated as an adjunct to diet to reduce triglyceride (TG) levels in adult patients with severe (greater than or equal to 500 mg per dL) hypertriglyceridemia (HTG).

Usage Considerations: Patients should be placed on an appropriate lipid-lowering diet before receiving LOVAZA and should continue this diet during treatment with LOVAZA.

Laboratory studies should be done to ascertain that the lipid levels are consistently abnormal before instituting therapy with LOVAZA. Every attempt should be made to control serum lipids with appropriate diet, exercise, weight loss in obese patients, and control of any medical problems such as diabetes mellitus and hypothyroidism that are contributing to the lipid abnormalities. Medications known to exacerbate hypertriglyceridemia (such as beta blockers, thiazides, estrogens) should be discontinued or changed if possible prior to consideration of triglyceride-lowering drug therapy.

Limitations of Use:

The effect of LOVAZA on the risk for pancreatitis has not been determined.

The effect of LOVAZA on cardiovascular mortality and morbidity has not been determined.

2 DOSAGE AND ADMINISTRATION

- Assess triglyceride levels carefully before initiating therapy. Identify other causes (e.g., diabetes mellitus, hypothyroidism, medications) of high triglyceride levels and manage as appropriate [see Indications and Usage (1)].
- Patients should be placed on an appropriate lipid-lowering diet before receiving LOVAZA, and should continue this diet during treatment with LOVAZA. In clinical studies, LOVAZA was administered with meals.

The daily dose of LOVAZA is 4 grams per day. The daily dose may be taken as a single 4-gram dose (4 capsules) or as two 2-gram doses (2 capsules given twice daily).

Patients should be advised to swallow LOVAZA capsules whole. Do not break open, crush, dissolve, or chew LOVAZA.

3 DOSAGE FORMS AND STRENGTHS

LOVAZA (omega-3-acid ethyl esters) capsules are supplied as 1-gram transparent, soft-gelatin capsules filled with light-yellow oil and bearing the designation “GS FH2”.

4 CONTRAINDICATIONS

LOVAZA is contraindicated in patients with known hypersensitivity (e.g., anaphylactic reaction) to LOVAZA or any of its components.

5 WARNINGS AND PRECAUTIONS

5.1 Monitoring: Laboratory Tests

In patients with hepatic impairment, alanine aminotransferase (ALT) and aspartate aminotransferase (AST) levels should be monitored periodically during therapy with LOVAZA. In some patients, increases in ALT levels without a concurrent increase in AST levels were observed.

In some patients, LOVAZA increases LDL-C levels. LDL-C levels should be monitored periodically during therapy with LOVAZA.

Laboratory studies should be performed periodically to measure the patient’s TG levels during therapy with LOVAZA.

5.2 Fish Allergy

LOVAZA contains ethyl esters of omega-3 fatty acids (EPA and DHA) obtained from the oil of several fish sources. It is not known whether patients with allergies to fish and/or shellfish, are at increased risk of an allergic reaction to LOVAZA. LOVAZA should be used with caution in patients with known hypersensitivity to fish and/or shellfish.

5.3 Recurrent Atrial Fibrillation (AF) or Flutter

In a double-blind, placebo-controlled trial of 663 subjects with symptomatic paroxysmal AF (n = 542) or persistent AF (n = 121), recurrent AF or flutter was observed in subjects randomized to LOVAZA who received 8 grams per day for 7 days and 4 grams per day thereafter for 23 weeks at a higher rate relative to placebo. Subjects in this trial had median baseline triglycerides of 127 mg per dL, had no substantial structural heart disease, were taking no anti-arrhythmic therapy (rate control permitted), and were in normal sinus rhythm at baseline.

At 24 weeks, in the paroxysmal AF stratum, there were 129 (47%) first recurrent symptomatic AF or flutter events on placebo and 141 (53%) on LOVAZA [primary endpoint, HR 1.19; 95% CI: 0.93, 1.35]. In the persistent AF stratum, there were 19 (35%) events on placebo and 34 (52%) events on LOVAZA [HR 1.63; 95% CI: 0.91, 2.18]. For both strata combined, the HR was 1.25; 95% CI: 1.00, 1.40. Although the clinical significance of these results is uncertain, there is a possible association between LOVAZA and more frequent recurrences of symptomatic atrial fibrillation or flutter in patients with paroxysmal or persistent atrial fibrillation, particularly within the first 2 to 3 months of initiating therapy.

LOVAZA is not indicated for the treatment of AF or flutter.

6 ADVERSE REACTIONS

6.1 Clinical Trials Experience

Because clinical trials are conducted under widely varying conditions, adverse reaction rates observed in the clinical trials of a drug cannot be directly compared with rates in the clinical trials of another drug and may not reflect the rates observed in practice.

Adverse reactions reported in at least 3% and at a greater rate than placebo for subjects treated with LOVAZA based on pooled data across 23 clinical trials are listed in Table 1.

Table 1. Adverse Reactions Occurring at Incidence ≥3% and Greater than Placebo in Clinical Trials of LOVAZA
Adverse Reactiona | LOVAZA; (n = 655) |  | Placebo; (n = 370)
Adverse Reactiona | n | % | n | %
Eructation | 29 | 4 | 5 | 1
Dyspepsia | 22 | 3 | 6 | 2
Taste perversion | 27 | 4 | 1 | <1

a Trials included subjects with HTG and severe HTG.
Additional adverse reactions from clinical trials are listed below:

Digestive System

Constipation, gastrointestinal disorder and vomiting.

Metabolic and Nutritional Disorders

Increased ALT and increased AST.

Skin

Pruritus and rash.

6.2 Postmarketing Experience

In addition to adverse reactions reported from clinical trials, the events described below have been identified during post-approval use of LOVAZA. Because these events are reported voluntarily from a population of unknown size, it is not possible to reliably estimate their frequency or to always establish a causal relationship to drug exposure.

The following events have been reported: anaphylactic reaction, hemorrhagic diathesis.

7 DRUG INTERACTIONS

7.1 Anticoagulants or Other Drugs Affecting Coagulation

Some trials with omega-3-acids demonstrated prolongation of bleeding time. The prolongation of bleeding time reported in these trials has not exceeded normal limits and did not produce clinically significant bleeding episodes. Clinical trials have not been done to thoroughly examine the effect of LOVAZA and concomitant anticoagulants. Patients receiving treatment with LOVAZA and an anticoagulant or other drug affecting coagulation (e.g., anti-platelet agents) should be monitored periodically.

8 USE IN SPECIFIC POPULATIONS

8.1 Pregnancy

Pregnancy Category C: There are no adequate and well-controlled studies in pregnant women. It is unknown whether LOVAZA can cause fetal harm when administered to a pregnant woman or can affect reproductive capacity. LOVAZA should be used during pregnancy only if the potential benefit to the patient justifies the potential risk to the fetus.

Animal Data

Omega-3-acid ethyl esters have been shown to have an embryocidal effect in pregnant rats when given in doses resulting in exposures 7 times the recommended human dose of 4 grams per day based on a body surface area comparison.

In female rats given oral gavage doses of 100, 600, and 2,000 mg per kg per day beginning 2 weeks prior to mating and continuing through gestation and lactation, no adverse effects were observed in the high-dose group (5 times human systemic exposure following an oral dose of 4 grams per day based on body surface area comparison).

In pregnant rats given oral gavage doses of 1,000, 3,000, and 6,000 mg per kg per day from gestation Day 6 through 15, no adverse effects were observed (14 times human systemic exposure following an oral dose of 4 grams per day based on a body surface area comparison).

In pregnant rats given oral gavage doses of 100, 600, and 2,000 mg per kg per day from gestation Day 14 through lactation Day 21, no adverse effects were seen at 2,000 mg per kg per day (5 times the human systemic exposure following an oral dose of 4 grams per day based on a body surface area comparison). However, decreased live births (20% reduction) and decreased survival to postnatal Day 4 (40% reduction) were observed in a dose-ranging study using higher doses of 3,000 mg per kg per day (7 times the human systemic exposure following an oral dose of 4 grams per day based on a body surface area comparison).

In pregnant rabbits given oral gavage doses of 375, 750, and 1,500 mg per kg per day from gestation Day 7 through 19, no findings were observed in the fetuses in groups given 375 mg per kg per day (2 times human systemic exposure following an oral dose of 4 grams per day based on a body surface area comparison). However, at higher doses, evidence of maternal toxicity was observed (4 times human systemic exposure following an oral dose of 4 grams per day based on a body surface area comparison).

8.3 Nursing Mothers

Studies with omega-3-acid ethyl esters have demonstrated excretion in human milk. The effect of this excretion on the infant of a nursing mother is unknown; caution should be exercised when LOVAZA is administered to a nursing mother. An animal study in lactating rats given oral gavage ^14C-ethyl EPA demonstrated that drug levels were 6 to 14 times higher in milk than in plasma.

8.4 Pediatric Use

Safety and effectiveness in pediatric patients have not been established.

8.5 Geriatric Use

A limited number of subjects older than 65 years were enrolled in the clinical trials of LOVAZA. Safety and efficacy findings in subjects older than 60 years did not appear to differ from those of subjects younger than 60 years.

9 DRUG ABUSE AND DEPENDENCE

LOVAZA does not have any known drug abuse or withdrawal effects.

11 DESCRIPTION

LOVAZA, a lipid-regulating agent, is supplied as a liquid-filled gel capsule for oral administration. Each 1-gram capsule of LOVAZA contains at least 900 mg of the ethyl esters of omega-3 fatty acids sourced from fish oils. These are predominantly a combination of ethyl esters of eicosapentaenoic acid (EPA — approximately 465 mg) and docosahexaenoic acid (DHA — approximately 375 mg).

The empirical formula of EPA ethyl ester is C22H34O2, and the molecular weight of EPA ethyl ester is 330.51. The structural formula of EPA ethyl ester is:

The empirical formula of DHA ethyl ester is C24H36O2, and the molecular weight of DHA ethyl ester is 356.55. The structural formula of DHA ethyl ester is:

LOVAZA capsules also contain the following inactive ingredients: 4 mg α-tocopherol (in a carrier of soybean oil), and gelatin, glycerol, and purified water (components of the capsule shell).

12 CLINICAL PHARMACOLOGY

12.1 Mechanism of Action

The mechanism of action of LOVAZA is not completely understood. Potential mechanisms of action include inhibition of acyl-CoA:1,2-diacylglycerol acyltransferase, increased mitochondrial and peroxisomal β-oxidation in the liver, decreased lipogenesis in the liver, and increased plasma lipoprotein lipase activity. LOVAZA may reduce the synthesis of triglycerides in the liver because EPA and DHA are poor substrates for the enzymes responsible for TG synthesis, and EPA and DHA inhibit esterification of other fatty acids.

12.3 Pharmacokinetics

In healthy volunteers and in subjects with hypertriglyceridemia, EPA and DHA were absorbed when administered as ethyl esters orally. Omega-3-acids administered as ethyl esters (LOVAZA) induced significant, dose-dependent increases in serum phospholipid EPA content, though increases in DHA content were less marked and not dose-dependent when administered as ethyl esters.

Specific Populations

Age: Uptake of EPA and DHA into serum phospholipids in subjects treated with LOVAZA was independent of age (younger than 49 years versus 49 years and older).

Gender: Females tended to have more uptake of EPA into serum phospholipids than males. The clinical significance of this is unknown.

Pediatric: Pharmacokinetics of LOVAZA have not been studied.

Renal or Hepatic Impairment: LOVAZA has not been studied in patients with renal or hepatic impairment.

Drug-Drug Interactions

Simvastatin: In a 14-day trial of 24 healthy adult subjects, daily coadministration of simvastatin 80 mg with LOVAZA 4 grams did not affect the extent (AUC) or rate (Cmax) of exposure to simvastatin or the major active metabolite, beta-hydroxy simvastatin, at steady state.

Atorvastatin: In a 14-day trial of 50 healthy adult subjects, daily coadministration of atorvastatin 80 mg with LOVAZA 4 grams did not affect AUC or Cmax of exposure to atorvastatin, 2-hydroxyatorvastatin, or 4-hydroxyatorvastatin at steady state.

Rosuvastatin: In a 14-day trial of 48 healthy adult subjects, daily coadministration of rosuvastatin 40 mg with LOVAZA 4 grams did not affect AUC or Cmax of exposure to rosuvastatin at steady state.

In vitro studies using human liver microsomes indicated that clinically significant cytochrome P450-mediated inhibition by EPA/DHA combinations are not expected in humans.

13 NONCLINICAL TOXICOLOGY

13.1 Carcinogenesis, Mutagenesis, Impairment of Fertility

In a rat carcinogenicity study with oral gavage doses of 100, 600, and 2,000 mg per kg per day, males were treated with omega-3-acid ethyl esters for 101 weeks and females for 89 weeks without an increased incidence of tumors (up to 5 times human systemic exposures following an oral dose of 4 grams per day based on a body surface area comparison). Standard lifetime carcinogenicity bioassays were not conducted in mice.

Omega-3-acid ethyl esters were not mutagenic or clastogenic with or without metabolic activation in the bacterial mutagenesis (Ames) test with Salmonella typhimurium and Escherichia coli or in the chromosomal aberration assay in Chinese hamster V79 lung cells or human lymphocytes. Omega-3-acid ethyl esters were negative in the in vivo mouse micronucleus assay.

In a rat fertility study with oral gavage doses of 100, 600, and 2,000 mg per kg per day, males were treated for 10 weeks prior to mating and females were treated for 2 weeks prior to and throughout mating, gestation, and lactation. No adverse effect on fertility was observed at 2,000 mg per kg per day (5 times human systemic exposure following an oral dose of 4 grams per day based on a body surface area comparison).

14 CLINICAL STUDIES

14.1 Severe Hypertriglyceridemia

The effects of LOVAZA 4 grams per day were assessed in 2 randomized, placebo-controlled, double-blind, parallel-group trials of 84 adult subjects (42 on LOVAZA, 42 on placebo) with very high triglyceride levels. Subjects whose baseline triglyceride levels were between 500 and 2,000 mg per dL were enrolled in these 2 trials of 6 and 16 weeks’ duration. The median triglyceride and LDL-C levels in these subjects were 792 mg per dL and 100 mg per dL, respectively. Median HDL-C level was 23.0 mg per dL.

The changes in the major lipoprotein lipid parameters for the groups receiving LOVAZA or placebo are shown in Table 2.

Table 2. Median Baseline and Percent Change from Baseline in Lipid Parameters in Subjects with Severe Hypertriglyceridemia (≥500 mg per dL)
Parameter | LOVAZA; n = 42 |  | Placebo; n = 42 |  | Difference
Parameter | BL | % Change | BL | % Change
TG | 816 | -44.9 | 788 | +6.7 | -51.6
Non-HDL-C | 271 | -13.8 | 292 | -3.6 | -10.2
TC | 296 | -9.7 | 314 | -1.7 | -8.0
VLDL-C | 175 | -41.7 | 175 | -0.9 | -40.8
HDL-C | 22 | +9.1 | 24 | 0.0 | +9.1
LDL-C | 89 | +44.5 | 108 | -4.8 | +49.3

BL = Baseline (mg per dL); % Change = Median Percent Change from Baseline; Difference = LOVAZA Median % Change – Placebo Median % Change.

LOVAZA 4 grams per day reduced median TG, VLDL-C, and non-HDL-C levels and increased median HDL-C from baseline relative to placebo. Treatment with LOVAZA to reduce very high TG levels may result in elevations in LDL-C and non-HDL-C in some individuals. Patients should be monitored to ensure that the LDL-C level does not increase excessively.

The effect of LOVAZA on the risk of pancreatitis has not been determined.

The effect of LOVAZA on cardiovascular mortality and morbidity has not been determined.

16 HOW SUPPLIED/STORAGE AND HANDLING

Product: 17856-0084

NDC: 17856-0084-1 50 CAPSULE, LIQUID FILLED in a CUP, UNIT-DOSE

17 PATIENT COUNSELING INFORMATION

Advise the patient to read the FDA-approved patient labeling (Patient Information).

Information for Patients:

- LOVAZA should be used with caution in patients with known sensitivity or allergy to fish and/or shellfish [see Warnings and Precautions (5.2)].
- Advise patients that use of lipid-regulating agents does not reduce the importance of adhering to diet [see Dosage and Administration (2)].
- Advise patients not to alter LOVAZA capsules in any way and to ingest intact capsules only [see Dosage and Administration (2)].
- Instruct patients to take LOVAZA as prescribed. If a dose is missed, advise patients to take it as soon as they remember. However, if they miss one day of LOVAZA, they should not double the dose when they take it.

Manufactured for:

GlaxoSmithKline

Research Triangle Park, NC 27709

LOVAZA is a registered trademark of the GSK group of companies.

©2015 the GSK group of companies. All rights reserved.

LVZ:13PI

PHARMACIST-DETACH HERE AND GIVE INSTRUCTIONS TO PATIENT

_ _ _ _ _ _ _ _ _ _ _ _ _ _ _ _ _ _ _ _ _ _ _ _ _ _ _ _ _ _ _ _ _ _ _ _ _ _ _ _ _ _ __ _ _ _ _ _ _ _

PATIENT INFORMATION

LOVAZA® (lō-vā-ză)

(omega-3-acid ethyl esters)

capsules

Read this Patient Information before you start taking LOVAZA, and each time you get a refill. There may be new information. This information does not take the place of talking with your doctor about your medical condition or your treatment.

What is LOVAZA?

LOVAZA is a prescription medicine used along with a low fat and low cholesterol diet to lower very high triglyceride (fat) levels in adults.

It is not known if LOVAZA changes your risk of having inflammation of your pancreas (pancreatitis).

It is not known if LOVAZA prevents you from having a heart attack or stroke.

It is not known if LOVAZA is safe and effective in children.

Who should not take LOVAZA?

Do not take LOVAZA if you are allergic to omega-3-acid ethyl esters or any of the ingredients in LOVAZA. See the end of this leaflet for a complete list of ingredients in LOVAZA.

What should I tell my doctor before taking LOVAZA?

Before you take LOVAZA, tell your doctor if you:

- have diabetes.
- have a low thyroid problem (hypothyroidism).
- have a liver problem.
- have a pancreas problem.
- have a certain heart rhythm problem called atrial fibrillation or flutter.
- are allergic to fish or shellfish. It is not known if people who are allergic to fish or shellfish are also allergic to LOVAZA.
- are pregnant or plan to become pregnant. It is not known if LOVAZA will harm your unborn baby.
- are breastfeeding or plan to breastfeed. LOVAZA can pass into your breast milk. You and your doctor should decide if you will take LOVAZA or breastfeed.

Tell your doctor about all the medicines you take, including prescription and over-the-counter medicine, vitamins, and herbal supplements.

LOVAZA can interact with certain other medicines that you are taking. Using LOVAZA with medicines that affect blood clotting (anticoagulants or blood thinners) may cause serious side effects.

Know the medicines you take. Keep a list of them to show your doctor and pharmacist when you get a new medicine.

How should I take LOVAZA?

- Take LOVAZA exactly as your doctor tells you to take it.
- You should not take more than 4 capsules of LOVAZA each day. Either take all 4 capsules at one time, or 2 capsules two times a day.
- Do not change your dose or stop LOVAZA without talking to your doctor.
- Take LOVAZA with or without food.
- Take LOVAZA capsules whole. Do not break, crush, dissolve, or chew LOVAZA capsules before swallowing. If you cannot swallow LOVAZA capsules whole, tell your doctor. You may need a different medicine.
- Your doctor may start you on a diet that is low in saturated fat, cholesterol, carbohydrates, and low in added sugars before giving you LOVAZA. Stay on this diet while taking LOVAZA.
- Your doctor should do blood tests to check your triglyceride, bad cholesterol and liver function levels while you take LOVAZA.

What are the possible side effects of LOVAZA?

LOVAZA may cause serious side effects, including:

- increases in the results of blood tests used to check your liver function (ALT and AST) and your bad cholesterol levels (LDL-C).
- increases in the frequency of a heart rhythm problem (atrial fibrillation or flutter) may especially happen in the first few months of taking LOVAZA if you already have that problem.

The most common side effects of LOVAZA include:

- burping
- upset stomach
- a change in your sense of taste.

Talk to your doctor if you have a side effect that bothers you or does not go away.

These are not all the possible side effects of LOVAZA. For more information, ask your doctor or pharmacist.

Call your doctor for medical advice about side effects. You may report side effects to FDA at 1-800-FDA-1088.

How should I store LOVAZA?

- Store LOVAZA at room temperature between 68°F to 77°F (20°C to 25°C).
- Do not freeze LOVAZA.
- Safely throw away medicine that is out of date or no longer needed.

Keep LOVAZA and all medicines out of the reach of children.

General information about the safe and effective use of LOVAZA

Medicines are sometimes prescribed for purposes other than those listed in a Patient Information leaflet. Do not use LOVAZA for a condition for which it was not prescribed. Do not give LOVAZA to other people, even if they have the same symptoms you have. It may harm them.

This Patient Information Leaflet summarizes the most important information about LOVAZA. If you would like more information, talk with your doctor. You can ask your doctor or pharmacist for information about LOVAZA that is written for health professionals.

For more information go to www.LOVAZA.com or call 1-888-825-5249.

What are the ingredients in LOVAZA?

Active Ingredient: omega-3-acid ethyl esters, mostly EPA and DHA

Inactive Ingredients: alpha-tocopherol (in soybean oil), gelatin, glycerol, purified water.

This patient labeling has been approved by the U.S. Food and Drug Administration.

Manufactured for:

GlaxoSmithKline

Research Triangle Park, NC 27709
LOVAZA is a registered trademark of the GSK group of companies.

©2015 the GSK group of companies. All rights reserved.

September 2015

LVZ:11PIL